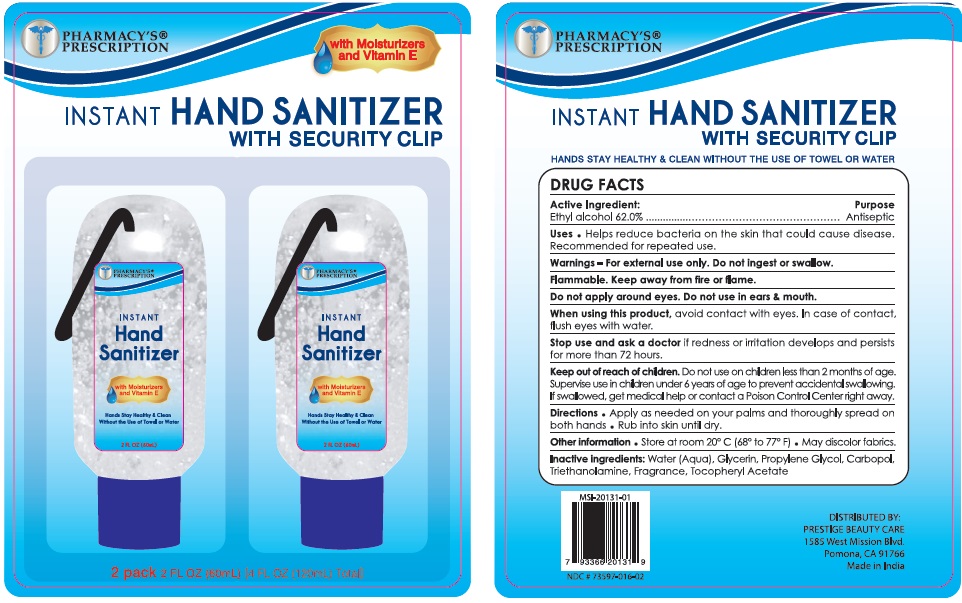 DRUG LABEL: PHARMACYS PRESCRIPTION INSTANT HAND SANITIZER-MOISTURIZERS AND VITAMIN E WITH SECURITY CLIP
NDC: 73398-111 | Form: GEL
Manufacturer: SUHAN AEROSOLS
Category: otc | Type: HUMAN OTC DRUG LABEL
Date: 20200810

ACTIVE INGREDIENTS: ALCOHOL 62 mL/100 mL
INACTIVE INGREDIENTS: WATER; GLYCERIN; PROPYLENE GLYCOL; CARBOMER HOMOPOLYMER, UNSPECIFIED TYPE; TROLAMINE; .ALPHA.-TOCOPHEROL ACETATE

Active Ingredient

Ethyl Alcohol 62% v/v.

Purpose

Antiseptic

Use

Help reduce bacteria on the skin that could cause disease. Recommended for repeated use.

Warnings

For external use only. Do not ingest or swallow.
Flammable. Keep away from fire or flame.
Do not apply around eyes. Do not use in ears & mouth.
When using this product, avoid contact with eyes. In case of contact, flush eyes with water.
Stop use and ask a doctor if redness or irritation develops and persists for more than 72 hours.

Keep out of reach of children. Do not use on children less than 2 months of age. Supervise use in children under 6 years of age to prevent accidental swallowing. If swallowed, get medical help or contact a Poison Control Center right away.

Directions

Apply as needed on your palms and thoroughly spread on both hands. Rub into skin until dry.

Other information

- Store at room 20° C (68° to 77°F)
- May discolor fabrics.

Inactive ingredients

Water (Aqua), Glycerin, Propylene Glycol, Carbopol, Triethanolamine, Fragrance, Tocopheryl Acetate